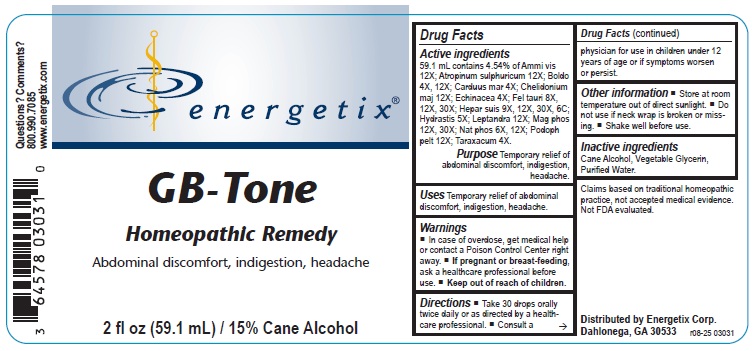 DRUG LABEL: GB-Tone
NDC: 64578-0159 | Form: LIQUID
Manufacturer: Energetix Corporation
Category: homeopathic | Type: HUMAN OTC DRUG LABEL
Date: 20251217

ACTIVE INGREDIENTS: VISNAGA DAUCOIDES FRUIT 12 [hp_X]/59.1 mL; ATROPINE SULFATE 12 [hp_X]/59.1 mL; PEUMUS BOLDUS LEAF 4 [hp_X]/59.1 mL; MILK THISTLE 4 [hp_X]/59.1 mL; CHELIDONIUM MAJUS 12 [hp_X]/59.1 mL; ECHINACEA, UNSPECIFIED 4 [hp_X]/59.1 mL; BOS TAURUS BILE 8 [hp_X]/59.1 mL; PORK LIVER 9 [hp_X]/59.1 mL; GOLDENSEAL 5 [hp_X]/59.1 mL; VERONICASTRUM VIRGINICUM ROOT 12 [hp_X]/59.1 mL; MAGNESIUM PHOSPHATE, DIBASIC TRIHYDRATE 12 [hp_X]/59.1 mL; SODIUM PHOSPHATE, DIBASIC, HEPTAHYDRATE 6 [hp_X]/59.1 mL; PODOPHYLLUM 12 [hp_X]/59.1 mL; TARAXACUM OFFICINALE 4 [hp_X]/59.1 mL
INACTIVE INGREDIENTS: ALCOHOL; GLYCERIN; WATER

GB-Tone

Active ingredients
59.1 mL contains 4.54% of Ammi vis 12X; Atropinum sulphuricum 12X; Boldo 4X, 12X; Carduus mar 4X; Chelidonium maj 12X; Echinacea 4X;
Fel tauri 8X, 12X, 30X; Hepar suis 9X, 12X, 30X, 6C; Hydrastis 5X; Leptandra 12X; Mag phos 12X, 30X; Nat phos 6X, 12X; Podoph pelt 12X;
Taraxacum 4X.

Claims based on traditional homeopathic practice, not accepted medical evidence. Not FDA evaluated.

INDICATIONS AND USAGE

UsesTemporary relief of abdominal discomfort, indigestion, headache.

Warnings

- In case of overdose, get medical help or contact a Poison Control Center right away.
- If pregnant or breast-feeding,ask a healthcare professional before use.

- Keep out of reach of children.

Directions

- Take 30 drops orally twice daily or as directed by a healthcare professional.
- Consult a physician for use in children under 12 years of age or if symptoms worsen or persist.

Other information

- Store room temperature out of direct sunlight.
- Do not use if neck wrap is broken or missing.
- Shake well before use.

Inactive ingredients
Cane Alcohol, Vegetable Glycerin, Purified Water.

QUESTIONS

Distributed by Energetix Corp.
Dahlonega, GA 30533
Questions? Comments?
800.990.7085
www.energetix.com

PACKAGE LABEL

energetix

GB-Tone

Homeopathic Remedy

Abdominal discomfort, indigestion, headache

2 fl oz (59.1 mL) / 15% Cane Alcohol

PURPOSE

Purpose Temporary relief of abdominal discomfort, indigestion, headache.